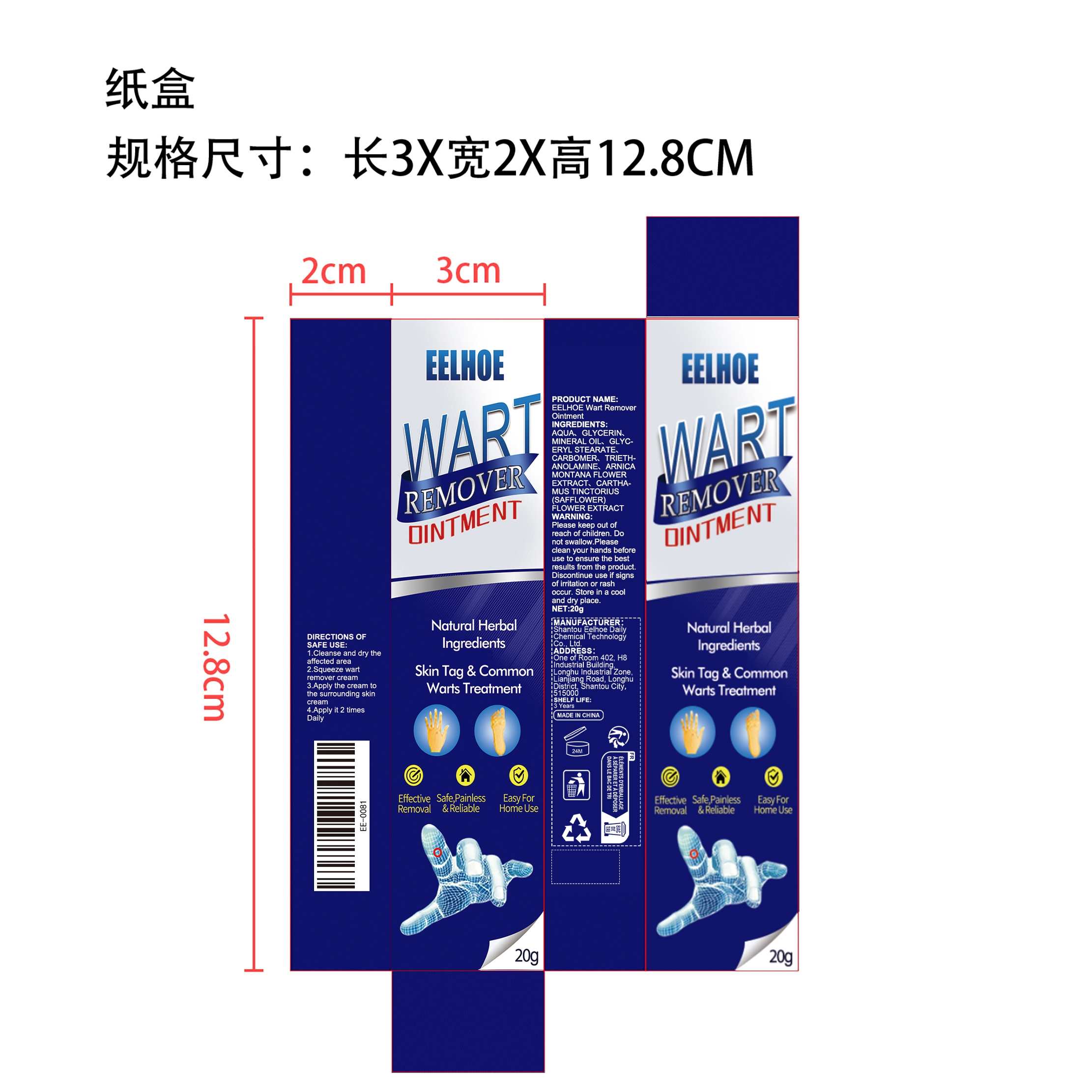 DRUG LABEL: EELHOE Wart Remover
NDC: 85064-005 | Form: OINTMENT
Manufacturer: Shantou Eelhoe Daily Chemical Technology Co., Ltd.
Category: otc | Type: HUMAN OTC DRUG LABEL
Date: 20251127

ACTIVE INGREDIENTS: SAFFLOWER 0.004 mg/20 mg; ARNICA MONTANA FLOWER 0.004 mg/20 mg
INACTIVE INGREDIENTS: AQUA 16.912 mg/20 mg; GLYCERYL STEARATE 0.4 mg/20 mg; MINERAL OIL 1 mg/20 mg; GLYCERIN 1.6 mg/20 mg; CARBOMER 0.04 mg/20 mg; TRIETHANOLAMINE 0.04 mg/20 mg

ACTIVE INGREDIENT

ARNICA MONTANA FLOWER
SAFFLOWER

PURPOSE

Natural Herbal Ingredients
Skin Tag & Common Warts Treatment

WHEN USING

1.Cleanse and dry the affected area.

2.Squeeze wart remover cream.

3.Apply the cream to the surrounding skin cream.

4.Apply it 2 times daily.

DO NOT USE

Discontinue use if signs of irritation or rash occur.

STOP USE

Discontinue use if signs of irritation or rash occur.

KEEP OUT OF REACH OF CHILDREN

Please keep out of reach of children. Do not swallow.

WARNINGS

Please keep out of reach of children. Do not swallow.Please clean your hands before use to ensure the best results from the product. Discontinue use if signs of irritation or rash occur. Store in a cool and dry place.

STORAGE AND HANDLING

Store in a cool and dry place.

INACTIVE INGREDIENT

AQUA、GLYCERIN、MINERAL OIL、GLYCERYL STEARATE、CARBOMER、TRIETHANOLAMINE